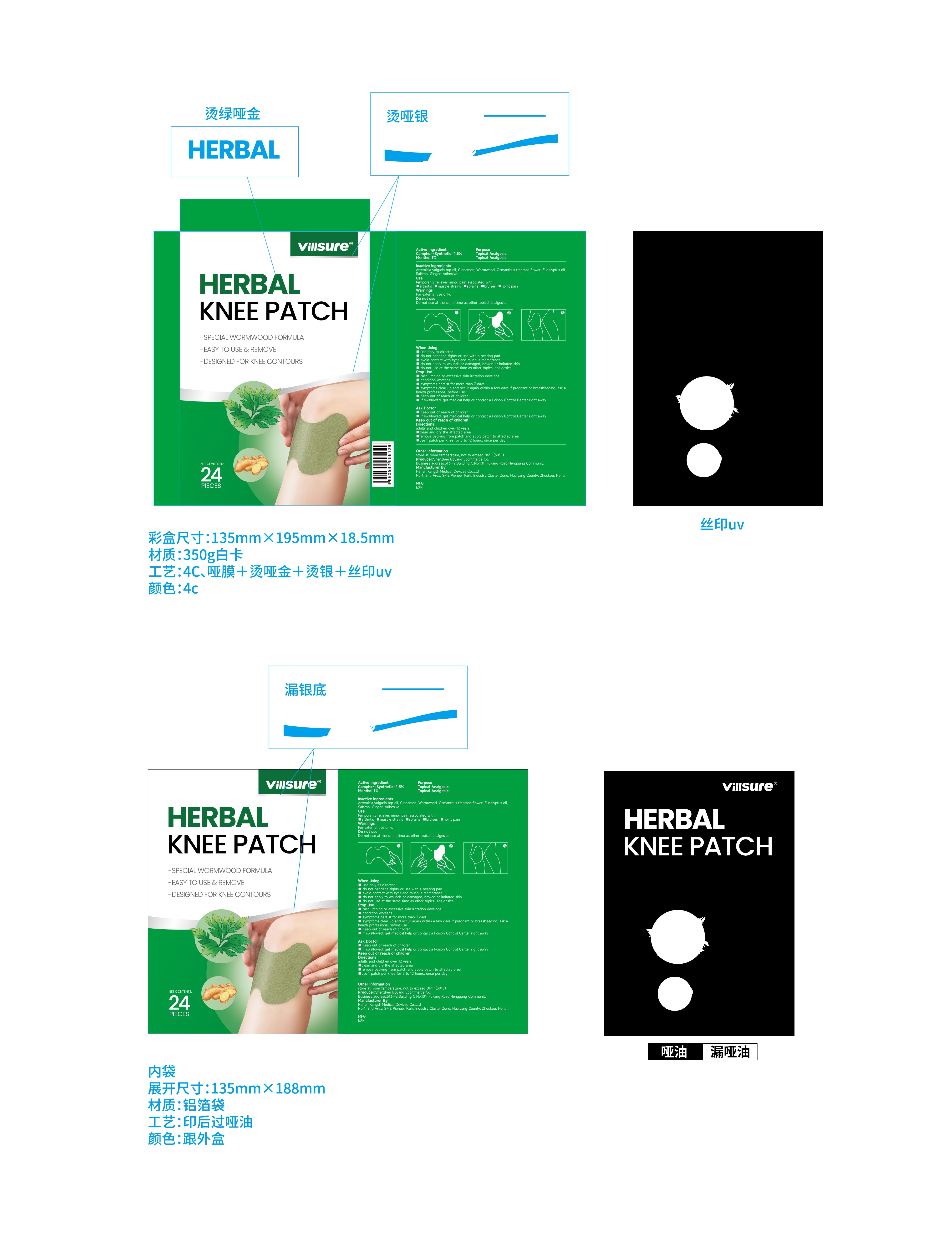 DRUG LABEL: Villsure HERBAL
NDC: 84716-006 | Form: PATCH
Manufacturer: Shenzhen Boyang E-commerce Co.
Category: otc | Type: HUMAN OTC DRUG LABEL
Date: 20241224

ACTIVE INGREDIENTS: CAMPHOR (SYNTHETIC) 0.015 [iU]/1 [iU]; MENTHOL 0.01 [iU]/1 [iU]
INACTIVE INGREDIENTS: CINNAMON OIL

ACTIVE INGREDIENTS

Camphor 1.5% 樟脑
Menthol 1%

PURPOSE

Topical Analgesic
temporarily relieves minor pain associated with:
arthritis,muscle strains,sprains,bruises,joint pain.

Uses

-EASY TO USE & REMOVE
-DESIGNED FOR KNEE CONTOURS

adults and children over 12 years;

clean and dry the affected area

remove backing from patch and apply patch to affected area

use 1 patch per knee for 8 to 12 hours, once per day

Warnings

For external use only.

Stop use and ask a doctor if

1.rash, itching or excessive skin irritation develops
2.condition worsens

3.symptoms persist for more than 7 days

4.symptoms clear up and occur again within a few days lf pregnant or breastfeeding, ask a health professional before use

5.Keep out of reach of children

6.If swallowed, get medical help or contact a Poison Control Center right away

Do not use at the same time as other topical analgesics
rash, itching or excessive skin irritation develops
condition worsens

symptoms persist for more than 7 days

symptoms clear up and occur again within a few days lf pregnant or breastfeeding, ask ahealth professional before use

Keep out of reach of children

If swallowed, get medical help or contact a Poison Control Center right away

Keep out of reach of children.

If swallowed, get medical help or contact a Poison Control Center right away

When using this product

1.use only as directed
2.do not bandage tighty or use with a heating pad

3.avoid contact with eyes and mucous membranes

4.do not apply to wounds or damaged, broken or imitated skin

5.do not use at the same time as other topical analgesics

INACTIVE INGREDIENT SECTON

CINNAMON OIL
ANREDERA CORDIFOLIA LEAF
TURPENTINE
CAPSICUM
LAUROCAPRAM
HOODIA GORDONII SAP
GRASS CARP

uses and storage method

Directions

adults and children over 12 years;

clean and dry the affected area

remove backing from patch and apply patch to affected area

use 1 patch per knee for 8 to 12 hours, once per day
Other information
store at room temperature, not to exceed 86°F(30°C)